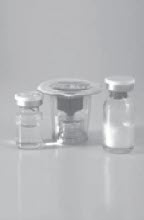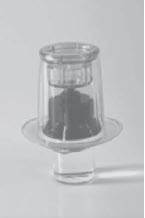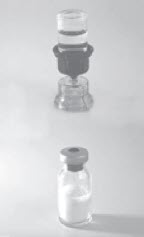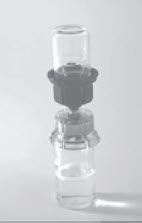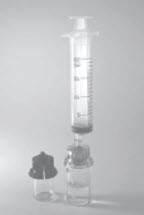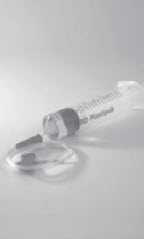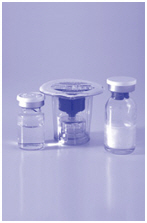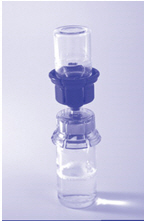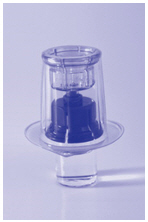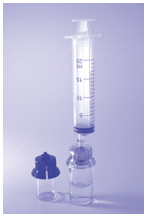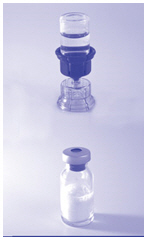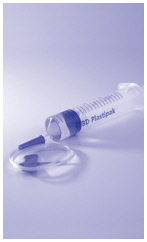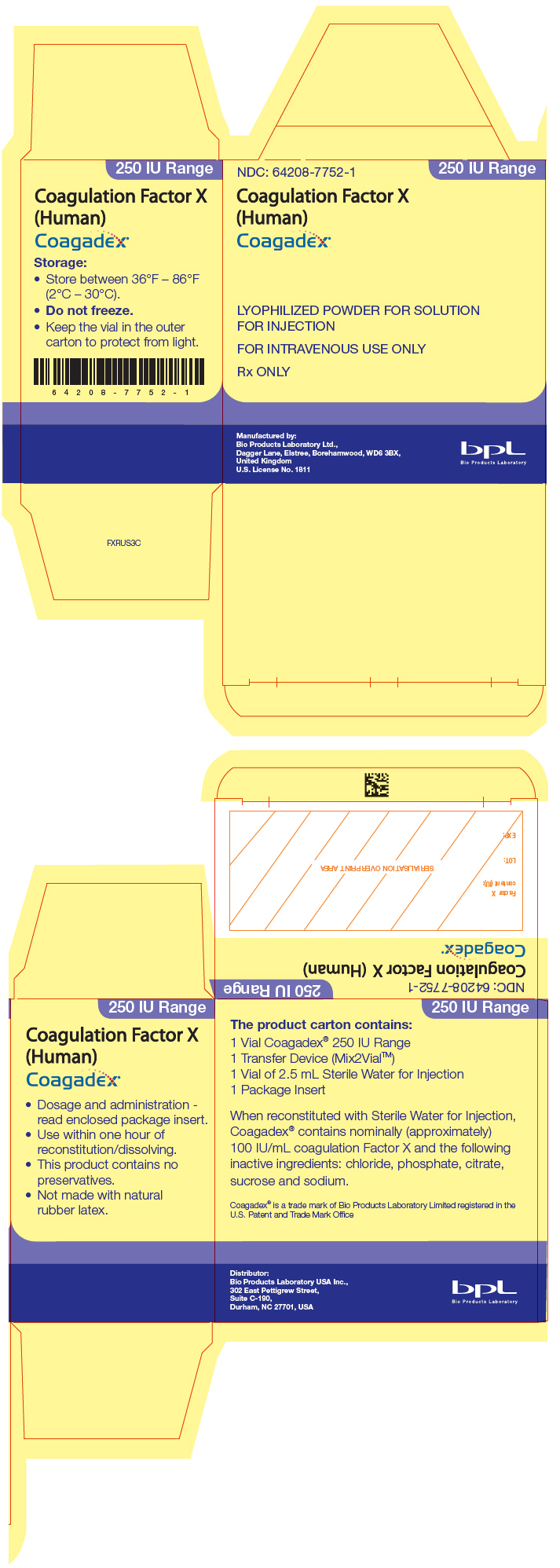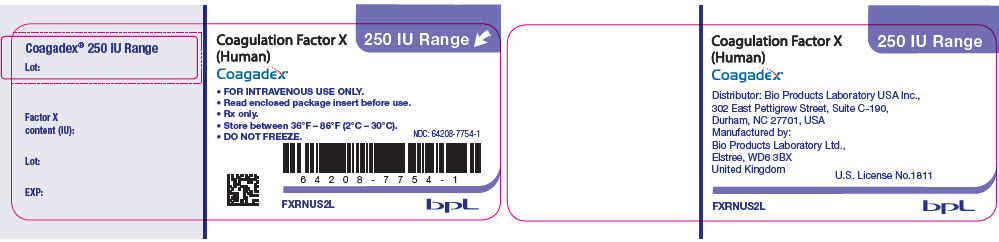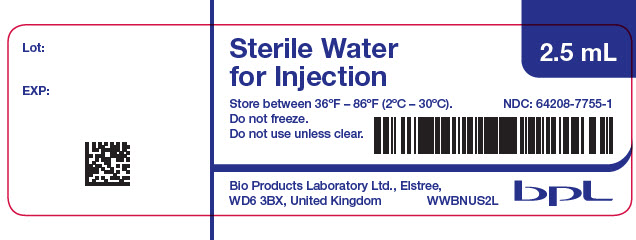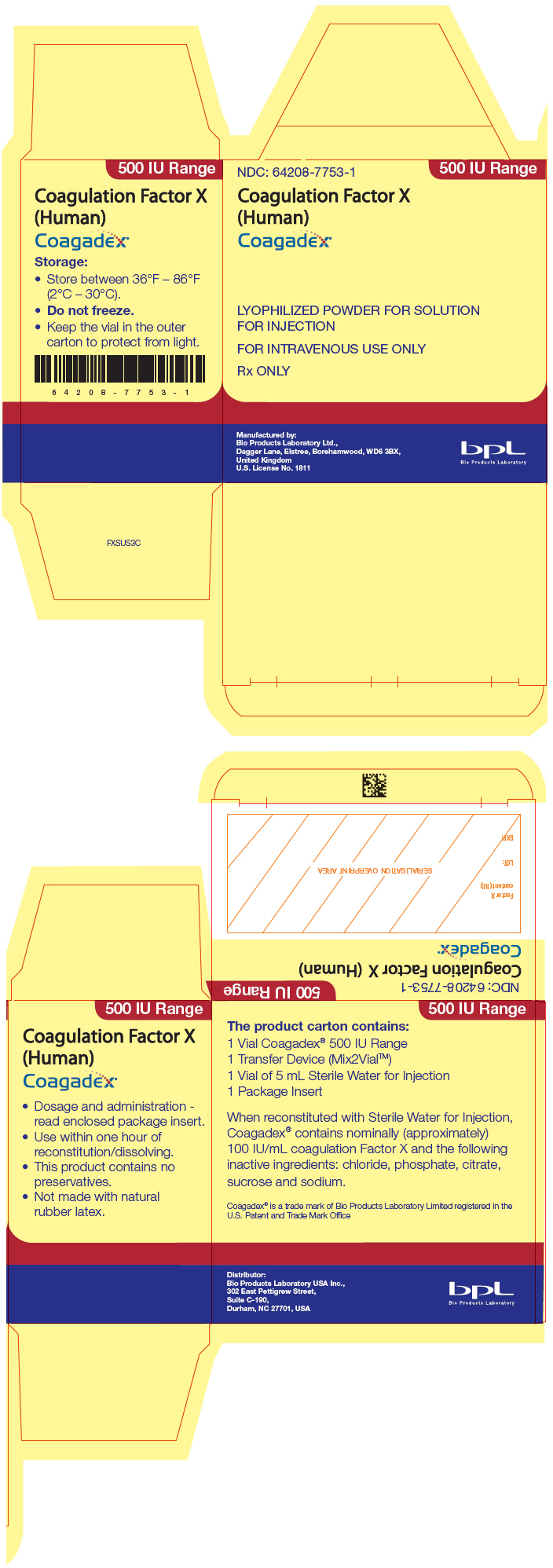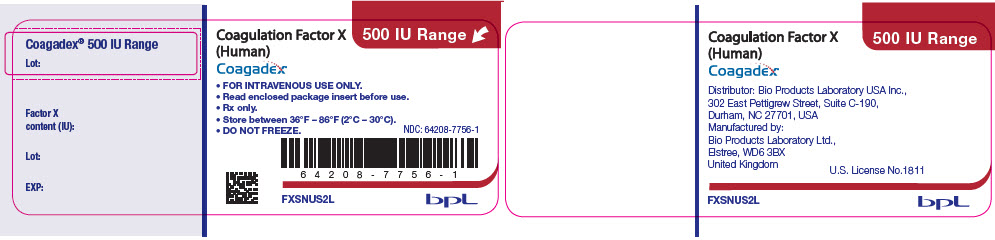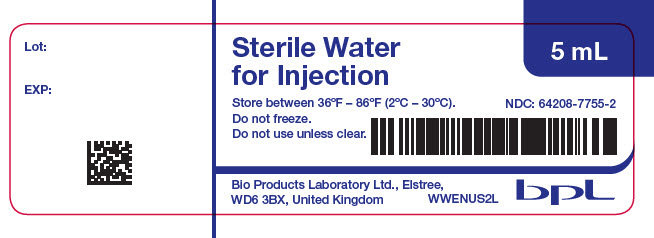 DRUG LABEL: Coagadex
NDC: 64208-7752 | Form: KIT | Route: INTRAVENOUS
Manufacturer: Bio Products Laboratory Ltd
Category: prescription | Type: HUMAN PRESCRIPTION DRUG LABEL
Date: 20251029

ACTIVE INGREDIENTS: COAGULATION FACTOR X HUMAN 100 [iU]/1 mL
INACTIVE INGREDIENTS: WATER

HIGHLIGHTS OF PRESCRIBING INFORMATION

These highlights do not include all the information needed to use COAGADEX® safely and effectively. See full prescribing information for COAGADEX®.
COAGADEX® (Coagulation Factor X (Human))
Lyophilized Powder for Solution for Intravenous Injection
Initial U.S. Approval: [2015]

RECENT MAJOR CHANGES

INDICATIONS AND USAGE (1) | 4/2023
DOSAGE AND ADMINISTRATION (2, 2.1, 2.3) | 4/2023

1 INDICATIONS AND USAGE

COAGADEX, Coagulation Factor X (Human), is a plasma-derived human blood coagulation factor indicated in adults and children with hereditary Factor X deficiency for:

- Routine prophylaxis to reduce the frequency of bleeding episodes (1)
- On-demand treatment and control of bleeding episodes (1)
- Perioperative management of bleeding in patients with mild, moderate and severe hereditary Factor X deficiency (1)

2 DOSAGE AND ADMINISTRATION

For intravenous use only after reconstitution.

- Each vial of COAGADEX contains the labeled amount of Factor X in international units (IU) (2)
- The dosage and duration of treatment depend on the severity of the Factor X deficiency, the location and extent of the bleeding and the patient's clinical condition (2.1)
- For prophylaxis of bleeding episodes (2.1):

Age | Initial dose | Further management
Children: Less than 12 years of age | 40 IU/kg twice weekly | Monitor trough blood levels of Factor X targeting ≥5 IU/dL and adjust dosage to clinical response and trough levels. Do not exceed a peak level of 120 IU/dL.
Adults and adolescents: 12 years of age or older | 25 IU/kg twice weekly | Monitor trough blood levels of Factor X targeting ≥5 IU/dL and adjust dosage to clinical response and trough levels. Do not exceed a peak level of 120 IU/dL.

- For treatment of bleeding episodes (2.1):

Age | Initial dose | Further management
Children: Less than 12 years of age | 30 IU/kg | Infuse at first sign of bleeding. Repeat at intervals of 24 hours until the bleed stops.
Adults and adolescents: 12 years of age or older | 25 IU/kg | Infuse at first sign of bleeding. Repeat at intervals of 24 hours until the bleed stops.

- For perioperative management (2.1):

Age | Initial dose | Further management
Children: Less than 12 years of age | Use a factor of 0.6 to calculate the required dose | Pre-surgery: raise plasma Factor X levels to 70-90 IU/dL. Post-surgery: maintain plasma Factor X levels at ≥50 IU/dL until the patient is no longer at risk of bleeding due to surgery.
Dose (IU) = body weight (kg) × desired factor X rise† (IU/dL or % of normal) × 0.6 |  | Pre-surgery: raise plasma Factor X levels to 70-90 IU/dL. Post-surgery: maintain plasma Factor X levels at ≥50 IU/dL until the patient is no longer at risk of bleeding due to surgery.
Adults and adolescents: 12 years of age or older | Use a factor of 0.5 to calculate the required dose | Pre-surgery: raise plasma Factor X levels to 70-90 IU/dL. Post-surgery: maintain plasma Factor X levels at ≥50 IU/dL until the patient is no longer at risk of bleeding due to surgery.
Dose (IU) = body weight (kg) × desired factor X rise‡ (IU/dL or % of normal) × 0.5 |  | Pre-surgery: raise plasma Factor X levels to 70-90 IU/dL. Post-surgery: maintain plasma Factor X levels at ≥50 IU/dL until the patient is no longer at risk of bleeding due to surgery.

3 DOSAGE FORMS AND STRENGTHS

COAGADEX is available as a lyophilized powder for reconstitution in single-dose vials containing nominally (approximately) 250 IU or 500 IU of Factor X activity. When reconstituted using the Sterile Water for Injection supplied with the kit, the final concentration is approximately 100 IU/mL (3).

4 CONTRAINDICATIONS

Do not use in patients who have had life-threatening hypersensitivity reactions to COAGADEX (4).

5 WARNINGS AND PRECAUTIONS

- Hypersensitivity reactions, including anaphylaxis, are possible. Should symptoms occur, discontinue COAGADEX and administer appropriate treatment (5.1).
- Development of neutralizing antibodies (inhibitors) may occur. If expected plasma Factor X activity levels are not attained, or if bleeding is not controlled with an appropriate dose, perform an assay that measures Factor X inhibitor concentration (5.2).
- COAGADEX is made from human blood and therefore carries a risk of transmitting infectious agents, e.g. viruses, the variant Creutzfeldt-Jakob disease (vCJD) agent and, theoretically, the Creutzfeldt-Jakob disease (CJD) agent (5.4).

6 ADVERSE REACTIONS

The most common adverse drug reactions (frequency ≥ 5% of subjects) observed in clinical trials were infusion site erythema, infusion site pain, fatigue and back pain (6).

To report SUSPECTED ADVERSE REACTIONS, contact BPL USA Inc., at 1-844-427-5872 or medinfo@bpl-us.com or FDA at 1-800-FDA-1088 or www.fda.gov/medwatch.

FULL PRESCRIBING INFORMATION

1 INDICATIONS AND USAGE

COAGADEX, Coagulation Factor X (Human), is a plasma-derived human blood coagulation Factor indicated in adults and children with hereditary Factor X deficiency for:

- Routine prophylaxis to reduce the frequency of bleeding episodes
- On-demand treatment and control of bleeding episodes
- Perioperative management of bleeding in patients with mild, moderate, and severe hereditary Factor X deficiency

2 DOSAGE AND ADMINISTRATION

For intravenous use after reconstitution only

2.1 Dose

- Dose and duration of the treatment depend on the severity of the Factor X deficiency, location and extent of the bleeding, the patient's age (<12 years or >12 years) and the patient's clinical condition.
- Base the dose and frequency on the individual clinical response. Do not administer more than 60 IU/kg daily.
- Each vial of COAGADEX is labeled with the actual Factor X potency/content in International Units (IU).

Prophylaxis of bleeding episodes
Age | Initial dose | Further management
Children: Less than 12 years of age | 40 IU/kg twice weekly | Due to inter-and intra-patient variability, it is recommended that trough blood levels of Factor X should be monitored at intervals, especially in the first weeks of therapy or after dosages changes. Adjust dosage regimen to clinical response and trough levels of Factor X of at least 5 IU/dL. Do not exceed a peak level of 120 IU/dL. [For more detailed calculations of dose, see Detailed Dose Calculation (2.1)].
Adults and adolescents: 12 years of age or older | 25 IU/kg twice weekly | Due to inter-and intra-patient variability, it is recommended that trough blood levels of Factor X should be monitored at intervals, especially in the first weeks of therapy or after dosages changes. Adjust dosage regimen to clinical response and trough levels of Factor X of at least 5 IU/dL. Do not exceed a peak level of 120 IU/dL. [For more detailed calculations of dose, see Detailed Dose Calculation (2.1)].

On–demand treatment and control of bleeding episodes
Age | Initial dose | Further management
Children: Less than 12 years of age | 30 IU/kg | Infuse COAGADEX when the first sign of bleeding occurs [see Clinical Trial Experience (6.1)]. Repeat at intervals of 24 hours until the bleed stops. [For more detailed calculations of dose, see Detailed Dose Calculation (2.1)].
Adults and adolescents: 12 years of age or older | 25 IU/kg | Infuse COAGADEX when the first sign of bleeding occurs [see Clinical Trial Experience (6.1)]. Repeat at intervals of 24 hours until the bleed stops. [For more detailed calculations of dose, see Detailed Dose Calculation (2.1)].

Perioperative management of bleeding
Age | Initial dose | Further management
Children: Less than 12 years of age | Use a factor of 0.6 to calculate the required dose | Measure post-infusion plasma Factor X levels for each patient before and after surgery to ensure that hemostatic levels are obtained and maintained. Pre-surgery: calculate the dose of COAGADEX to raise plasma Factor X levels to 70-90 IU/dL Post-surgery: Repeat dose as necessary to maintain plasma Factor X levels at a minimum of 50 IU/dL until the patient is no longer at risk of bleeding due to surgery
Dose (IU) = body weight (kg) × desired factor X rise† (IU/dL or % of normal) × 0.6 |  | Measure post-infusion plasma Factor X levels for each patient before and after surgery to ensure that hemostatic levels are obtained and maintained. Pre-surgery: calculate the dose of COAGADEX to raise plasma Factor X levels to 70-90 IU/dL Post-surgery: Repeat dose as necessary to maintain plasma Factor X levels at a minimum of 50 IU/dL until the patient is no longer at risk of bleeding due to surgery
Adults and adolescents: 12 years of age or older | Use a factor of 0.5 to calculate the required dose | Measure post-infusion plasma Factor X levels for each patient before and after surgery to ensure that hemostatic levels are obtained and maintained. Pre-surgery: calculate the dose of COAGADEX to raise plasma Factor X levels to 70-90 IU/dL Post-surgery: Repeat dose as necessary to maintain plasma Factor X levels at a minimum of 50 IU/dL until the patient is no longer at risk of bleeding due to surgery
Dose (IU) = body weight (kg) × desired factor X rise‡ (IU/dL or % of normal) × 0.5

Detailed Dose Calculation

- For young children (less than 12 years of age), the incremental recovery is approximately 1.7 IU/dL per IU/kg so the number at the end of each of the above formulae changes as follows:
  Dose (IU) = Body Weight (kg) × Desired Factor X Rise (IU/dL) × 0.6
  †The desired Factor X rise is the difference between the patient's plasma Factor X level and the maximum desired level.
  To estimate the expected in vivo maximum increase in plasma Factor X, expressed as IU/dL (or % of normal), use the following formula:
  Estimated Increment of Factor X (IU/dL or % of normal) = [Total Dose (IU)/Body Weight (kg)] × 1.7
- For adolescents and adults (at least 12 years of age), the incremental recovery is approximately 2.0 IU/dL per IU/kg so the number at the end of each of the above formulae changes as follows:
  Dose (IU) = Body Weight (kg) × Desired Factor X Rise (IU/dL or % of normal) × 0.5
  ‡The desired Factor X rise is the difference between the patient's plasma Factor X level and the maximum desired level.
  To estimate the expected in vivo maximum increase in plasma Factor X expressed as IU/dL (or % of normal) use the following formula:
  Estimated Increment of Factor X (IU/dL or % of normal) = [Total Dose (IU)/Body Weight (kg)]× 2

2.2 Preparation and Reconstitution

- Always work on a clean surface and wash your hands before performing the following procedures.
- To reconstitute, use the diluent (Sterile Water for Injection) and transfer device (Mix2Vial) provided in the COAGADEX carton.
- To administer, you will also need a syringe and suitable needle (not provided in the COAGADEX carton).
- Bring the vials of COAGADEX and the Sterile Water for Injection to room temperature before mixing.
- The reconstitution is performed as follows:

Table 1 COAGADEX Reconstitution Instructions
 | Step 1; - Remove the cap from the vial of COAGADEX and clean the top of the rubber stopper with an alcohol swab (not supplied) and allow to dry prior to opening the Mix2Vial package. - Repeat this step with the vial of sterile water.; Step 2; - Peel back the top of the Mix2Vial package. Do not remove the device from the package.
 | Step 3; - Place the blue end of the Mix2Vial over the water vial and push straight down until the spike penetrates the rubber stopper and snaps into place. - Remove the plastic outer packaging from the Mix2Vial and discard it. Do not touch the exposed end of the device.
 | Step 4; - With the COAGADEX vial placed on a flat surface, invert the water vial with the Mix2Vial device still attached. - Place the clear end of the Mix2Vial on the product vial and push straight down until the spike penetrates the rubber stopper and snaps into place. - The water will automatically transfer into the COAGADEX vial by the vacuum contained within it. Do not use if the water is not pulled into the vial of COAGADEX.
 | Step 5; - Gently swirl the COAGADEX vial to make sure that the powder is fully dissolved. Do not shake the vial. - The reconstituted solution should be clear or a slightly pearl-like solution. Do not use if particulate matter or discoloration is observed and contact BPL.
 | Step 6; - Separate the empty water vial and blue part of the Mix2Vial from the clear part that is attached to the COAGADEX vial by unscrewing counter-clockwise.; Step 7; - Draw air into an empty, sterile syringe (not supplied) by pulling the plunger to the volume of water added. - Connect the syringe to the clear part of the Mix2Vial and push the air in the syringe into the vial.
 | Step 8; - Immediately invert the COAGADEX vial. The solution will automatically be drawn into the syringe. Draw the remaining solution into the syringe by pulling the plunger back slowly. - Disconnect the filled syringe from the device. - Use the product immediately after reconstitution. Do not store the reconstituted product.

2.3 Administration

For intravenous administration only

- If the dose requires more than one vial of COAGADEX:
  - Reconstitute each vial (steps 1 to 5) using a new Mix2Vial for each vial
  - Draw up all of the solution into a single syringe (steps 6 to 8)
- Visually inspect the final solution for particulate matter and discoloration prior to administration. Do not use if particulate matter or discoloration is observed
- Attach a suitable needle to the syringe
- Administer by intravenous infusion at a rate of 10 mL/min, but no more than 20 mL/min

3 DOSAGE FORMS AND STRENGTHS

COAGADEX is available as a white or off-white lyophilized powder for reconstitution in single-dose vials containing nominally (approximately) 250 IU or 500 IU of Factor X activity. The exact potency/content is listed on the vial label. When reconstituted using the Sterile Water for Injection supplied with the kit, the final concentration is approximately 100 IU/mL.

Factor X activity in COAGADEX is defined in IU and determined using an in vitro chromogenic assay and a Factor X concentrate reference standard calibrated against the current World Health Organization (WHO) International Standard for Blood Coagulation Factors II and X, Concentrate.

4 CONTRAINDICATIONS

COAGADEX is contraindicated in patients who have had life-threatening hypersensitivity reactions to COAGADEX [see Description (11)].

5 WARNINGS AND PRECAUTIONS

5.1 Hypersensitivity Reactions

Allergic type hypersensitivity reactions, including anaphylaxis, are possible. Early signs of hypersensitivity reactions including angioedema, infusion site inflammation (e.g. burning, stinging, erythema), chills, cough, dizziness, fever, flushing, generalized urticaria, headache, hives, hypotension, lethargy, musculoskeletal pains, nausea, pruritus, rash, restlessness, tachycardia, tightness of the chest, tingling, vomiting, wheezing. If hypersensitivity symptoms occur, discontinue use of the product immediately and administer appropriate emergency treatment.

COAGADEX contains traces of human proteins other than Factor X.

5.2 Neutralizing Antibodies

The formation of neutralizing antibodies (inhibitors) to Factor X may occur. Monitor all patients treated with COAGADEX for the development of inhibitors by appropriate clinical observations and laboratory tests. If expected Factor X activity levels are not attained, or if bleeding is not controlled with an expected dose, perform an assay that measures Factor X inhibitor concentration.

5.3 Transmissible Infectious Agents

As COAGADEX is made from human blood, it may carry a risk of transmitting infectious agents, e.g. viruses, the variant Creutzfeldt-Jakob disease (vCJD) agent and, theoretically, the Creutzfeldt-Jakob disease (CJD) agent. There is also the possibility that unknown infectious agents may be present in the product. The risk that the product will transmit viruses has been reduced by screening plasma donors for prior exposure to certain viruses, by testing for the presence of certain current virus infections, and by inactivating and removing certain viruses during manufacture. Despite these measures, this product may still potentially transmit diseases.

All infections suspected by a physician possibly to have been transmitted by this product should be reported by the physician or other healthcare providers to BPL USA Inc. at 1-844-427-5872 or medinfo@bpl-us.com.

5.4 Monitoring and Laboratory Tests

- Monitor plasma Factor X activity by performing a validated test (e.g. one-stage clotting assay), to confirm that adequate Factor X levels have been achieved and maintained [see Dosage and Administration (2)].
- Monitor for the development of Factor X inhibitors. Perform a Nijmegen-Bethesda inhibitor assay if expected Factor X plasma levels are not attained, or if bleeding is not controlled with the expected dose of COAGADEX. Use Nijmegen-Bethesda Units (BU) to report inhibitor levels.

6 ADVERSE REACTIONS

The most common adverse drug reactions (frequency ≥ 5% of subjects) observed in clinical trials were infusion site erythema, infusion site pain, fatigue, and back pain.

6.1 Clinical Trials Experience

As clinical trials are conducted under widely varying conditions, adverse reaction rates observed in the clinical trials of a drug cannot be directly compared to rates in the clinical trial of another drug and may not reflect the rates observed in clinical practice.

During the clinical development of COAGADEX involving three multicenter, open-label, non-randomized clinical studies, 27 individual subjects with hereditary Factor X deficiency received at least one dose of COAGADEX.

Sixteen subjects aged 12 to 58 years with moderate to severe hereditary Factor X deficiency (basal FX:C < 5 IU/dL) received doses of COAGADEX for pharmacokinetic evaluation, on-demand treatment for control of bleeding episodes, and/or perioperative management of minor surgical or dental procedures. A total of 468 infusions were administered, including 242 for on-demand treatment and control of bleeding episodes, 6 for perioperative management and 31 for PK assessments. Spontaneous, traumatic and menorrhagic bleeding episodes were treated with an on-demand dose of 25 IU/kg for up to 2 years.

Two subjects aged 55 and 59 years with mild hereditary Factor X deficiency (basal FX:C 6 IU/dL and 8 IU/dL) received COAGADEX for perioperative management of four major surgical procedures. There were 40 exposure days to COAGADEX.

Six adverse reactions were reported in 2 of the 18 subjects. These were infusion site erythema (2 reports in 1 subject [5.6%]), fatigue (2 reports in 1 subject [5.6%]), back pain (1 report [5.6%]) and infusion site pain (1 report [5.6%]).

In a separate study, nine children (aged 2 to 11 years), of whom four were less than 6 years of age, received 537 (mean 59.7) doses of COAGADEX as routine prophylaxis of bleeding episodes during a period of at least 6 months. In addition, 22 infusions were given to treat a bleed, equivalent to 2.1 bleeds per subject per year. There were no adverse drug reactions in this study.

6.2 Immunogenicity

Immunogenicity was evaluated in three studies and all subjects (adults and children) underwent Factor X inhibitor testing (inhibitor screen and Nijmegen-Bethesda assay) at baseline, end of study and at 3-monthly intervals in between. For subjects who underwent surgery, inhibitor testing was done pre-surgery and on discharge. All inhibitor tests were negative. Additionally, comparison of pharmacokinetic (PK) parameters at the repeat PK assessment with those at first dose did not suggest development of any inhibitors to Factor X.

The detection of antibody formation is highly dependent on the sensitivity and specificity of the assay. Additionally, the observed incidence of antibody (including neutralizing antibody) positivity in an assay may be influenced by several factors including assay methodology, sample handling, timing of sample collection, concomitant medications, and underlying disease. For these reasons, it may be misleading to compare the incidence of antibodies to COAGADEX in the studies described above with the incidence of antibodies in other studies or to other products.

7 DRUG INTERACTIONS

Drug interaction studies have not been performed. Use with caution in patients who are receiving other plasma products that may contain Factor X (e.g. fresh frozen plasma, prothrombin complex concentrates). Based on the mechanism of action, COAGADEX is likely to be counteracted by direct and indirect Factor Xa inhibitors [see Clinical Pharmacology (12.1)].

8 USE IN SPECIFIC POPULATIONS

8.1 Pregnancy

Risk Summary

There is limited data with COAGADEX in pregnant women to inform on drug-associated risk. Animal reproduction studies have not been conducted using COAGADEX. It is not known whether COAGADEX can cause fetal harm when administered to a pregnant woman or can affect reproduction capacity. In the U.S. general population, the estimated background risk of major birth defects and miscarriage in clinically recognized pregnancies is 2-4% and 15-20%, respectively.

8.2 Lactation

Risk Summary

There is no information regarding the presence of COAGADEX in human milk, the effects on the breast-fed infant, or the effects on milk production. The developmental and health benefits of breast-feeding should be considered along with the mother's clinical need for COAGADEX and any potential adverse effects on the breast-fed infant from COAGADEX or from the underlying maternal condition.

8.4 Pediatric Use

A prospective, open-label, multicenter study was conducted in nine pediatric patients (0-5 years, n=4; 6-11 years, n=5) with severe (n=8) or moderate (n=1) hereditary factor X deficiency, to assess safety, efficacy, and pharmacokinetics of COAGADEX used prophylactically and on-demand. Patients had baseline FX levels < 5 IU/dL, and were dosed to achieve post-treatment levels of at least 5 IU/dL. After ≥26 weeks and ≥50 exposure days, investigators rated pdFX efficacy for preventing/decreasing bleeds. At end of study, investigators rated pdFX efficacy excellent for all subjects. Ten bleeds occurred (n = 3 subjects; 6 major, 3 minor, 1 unassessed for severity). Trough FX:C levels remained >5 IU/dL for all subjects after achievement of steady state. All AEs were unrelated to treatment; no inhibitor development or clinically significant changes in laboratory parameters were observed.

Six additional pediatric subjects aged 12 to 17 years were included in a prospective, open-label, multicenter study of COAGADEX to treat spontaneous, traumatic and menorrhagic bleeding episodes. Overall efficacy and safety outcomes were comparable to those in the younger age groups. [See Clinical Trial Experience (6.1), Pharmacokinetics (12.3) and Clinical Studies (14)].

8.5 Geriatric Use

Clinical studies of COAGADEX did not include sufficient numbers of subjects aged 65 and over to determine whether they respond differently from younger subjects. Other reported clinical experience has not identified differences in responses between the elderly and younger patients. In general, dose selection for an elderly patient should be cautious, usually starting at the low end of the dosing range, reflecting the greater frequency of decreased hepatic, renal, or cardiac function, and of concomitant disease or other drug therapy.

10 OVERDOSAGE

One case of accidental overdosage was reported in the clinical trials, in which a subject received approximately 80 IU/kg Factor X to treat a bleed. No adverse events were reported relating to this overdose.

11 DESCRIPTION

COAGADEX is a plasma-derived, sterile, purified concentrate of human coagulation Factor X that contains sucrose as a stabilizer. It is formulated as a lyophilized powder for solution for intravenous administration. When reconstituted with Sterile Water for Injection it forms a colorless, clear or slightly pearl-like solution. COAGADEX contains nominally (approximately) 100 IU/mL of coagulation Factor X and the following inactive ingredients: chloride, phosphate, citrate, sucrose and sodium. Each vial of COAGADEX is labeled with the actual Factor X activity/content expressed in IU per vial. Factor X activity in IU is determined using an in vitro chromogenic assay and a Factor X concentrate reference standard calibrated against the current WHO International Standard for Blood Coagulation Factors II and X Concentrate.

COAGADEX contains no added biological components such as heparin, albumin or anti-thrombin. The content of Factor II and Factor IX are ≤ 1 IU/mL of the reconstituted product. Factor Xa and Factor IIa were not detectable by Non-activated Partial Thromboplastin Time (NaPTT) or Fibrinogen Clotting Time (FCT) tests for potential thrombogenicity, and comprised < 10 parts per million by weight when tested by more sensitive analytical methods. The specific activity of COAGADEX is typically 80-137 IU per mg protein. The product contains no preservatives.

COAGADEX is manufactured from plasma, obtained from healthy US donors, who have passed viral screening tests. All donors are subjected to medical examinations, laboratory tests, and a review of their medical history before being allowed to donate blood or plasma.

All plasma donations are screened for antibody to human immunodeficiency virus (HIV)-1/2, hepatitis C virus (HCV), and hepatitis B surface antigen (HBsAg). Additional testing of donations is carried out in plasma mini-pools (512 donations per pool) with nucleic acid amplification testing (NAT) for HIV, hepatitis B virus (HBV), hepatitis C virus (HCV), hepatitis A virus (HAV) and human parvovirus B19. Furthermore, each manufacturing pool is tested to be negative for HBsAg and anti-HIV-1/2 antibodies. Also, manufacturing pools are non-reactive by nucleic acid test for HAV, HBV, HCV, and HIV-1. The limit for human parvovirus B19 in the manufacturing pools is set not to exceed 10^4 IU/mL.

Three processing steps specifically designed to remove or inactivate viruses are:

1) Solvent/detergent treatment targeted to inactivate enveloped viruses

2) A 15-nm filtration step designed to remove small viruses including non-enveloped viruses

3) Terminal dry-heat treatment at 80°C for 72 hours in the final container to inactivate enveloped and non-enveloped viruses

The capacity of the manufacturing process to remove and/or inactivate enveloped and non-enveloped viruses has been validated by laboratory spiking studies on a scaled-down process model. Overall virus reduction was calculated only from steps that were mechanistically independent from each other. Table 2 presents the contribution of each process step to virus reduction and the overall process reduction.

Table 2 Viral Reduction by Process Step
 |  |  | Process Log10 Reduction of Virus (LRV) over manufacturing step
Virus | Type (Envelope/Genome) | Size (nm) | Solvent/detergent | 15-nm filtration | Terminal dry-heat treatment | Total LRV
HIV | Env/RNA | 80-100 | > 4.6 | > 6.8 | 5.5 | > 16.9
SIN | Env/RNA | 60-70 | 6.0 | NT | NT | 6.0
BVDV | Env/RNA | 50-70 | > 5.1 | > 4.5 | > 5.2 | > 14.8
HSV | Env/DNA | 120-200 | > 5.4 | 5.8 | 3.5 | > 14.7
IBR | Env/DNA | 120-200 | > 5.3 | NT | NT | > 5.3
WNV | Env/RNA | 40-60 | 4.9 | NT | NT | 4.9
HAV | Non-Env/RNA | 25-30 | NA | > 5.0 | > 6.1 | > 11.1
CPV | Non-Env/RNA | 18-24 | NA | 4.3 [Studies using human parvovirus B19, which are considered experimental in nature, have demonstrated a virus reduction factor of > 5.9 log10 by 15-nm filtration using a PCR method] | 4.2 | 8.5
HIV: Human immunodeficiency virus
SIN: Sindbis virus, model for HCV
WNV: West Nile Virus
BVDV: Bovine viral diarrhea virus, model for HCV
IBR: Infectious bovine rhinotracheitis, bovine herpes virus model for enveloped DNA viruses including HBV
HAV: Hepatitis A virus
HSV: Herpes simplex virus
CPV: Canine parvovirus, model for human parvovirus B19
NA: Not applicable, solvent/detergent treatment step is limited to the inactivation of enveloped viruses
NT: Not tested

12 CLINICAL PHARMACOLOGY

12.1 Mechanism of Action

COAGADEX temporarily replaces the missing Factor X needed for effective hemostasis. Factor X is an inactive zymogen, which can be activated by Factor IXa (via the intrinsic pathway) or by Factor VIIa (via the extrinsic pathway). Factor X is converted from its inactive form to the active form (Factor Xa) by the cleavage of a 52-residue peptide from the heavy chain. Factor Xa associates with Factor Va on a phospholipid surface to form the prothrombinase complex, which activates prothrombin to thrombin in the presence of calcium ions. Thrombin then acts upon soluble fibrinogen and Factor XIII to generate a cross-linked fibrin clot.

12.2 Pharmacodynamics

The administration of COAGADEX increases plasma levels of Factor X and can temporarily correct the coagulation defect in these patients, as reflected by decrease in the aPTT and PT.

12.3 Pharmacokinetics

In a clinical study of COAGADEX in subjects with severe or moderate Factor X deficiency (basal FX:C < 5 IU/dL), the pharmacokinetics of COAGADEX were assessed after intravenous infusion (mean [range] infusion rate 5.9 [1.3-17.1] mL/min) of 25 IU/kg COAGADEX. Pharmacokinetic (PK) parameters were calculated from plasma Factor X:C activity measurements after subtraction of the pre-dose value. The PK assessment was repeated at least 6 months after the first dose. The PK parameters following a single dose are summarized in Table 3. The pharmacokinetics of COAGADEX were similar following the single and repeat dosing.

Table 3 Mean PK Parameters of COAGADEX Following a Single 25 IU/kg Dose to Subjects 12 years of Age and Older
 | First Dose Mean (CV%) (n=16)
Cmax (IU/mL) | 0.504 (17.2)
Half-life (hr) | 30.3 (22.8)
AUC0-144h (IU.hr/mL) | 17.1 (21.0)
AUC(0-∞) (IU.hr/mL) | 18.0 (20.9)
Vss (mL/kg) | 56.3 (24.0)
CL (mL/kg/hr) | 1.35 (21.7)
MRT (hr) | 41.8 (21.7)
Incremental recovery (IU/dL per IU/kg) [Using peak increment within 30 minutes post-dose] | 2.04 (19.5)
CV: Coefficient of variation

Incremental recovery in children <12 years of age was assessed at baseline and 6 months after the first dose. Values are summarized in Table 4.

Table 4 Incremental Recovery (IU/mL per IU/kg) in Young Children Under 12 Years of Age
Pediatric age group | Visit 1 [First dose of COAGADEX;] Mean (Min-Max) | End of Study [After at least 6 months;] Mean (Min-Max)
Aged 6-11 years (n = 5) | 1.83 (1.6–2.2) | 1.99 (1.8–2.2)
Aged 0-5 years (n = 4) | 1.45 (1.3–1.6) | 1.62 (1.3–1.8)

Studies were not conducted to evaluate the impact of gender or renal/hepatic function on the pharmacokinetics of COAGADEX.

13 NONCLINICAL TOXICOLOGY

13.1 Carcinogenesis, Mutagenesis, Impairment of Fertility

Nonclinical studies evaluating the carcinogenic or mutagenic potential of COAGADEX have not been conducted. No animal studies regarding impairment of fertility following COAGADEX dosing were conducted; however, no macroscopic or microscopic pathologies in reproductive organs were observed in rats dosed every other day with 6 times the maximum recommended clinical dose of 60 IU/kg COAGADEX for 28 days.

14 CLINICAL STUDIES

Prophylaxis of Bleeding Episodes

In a multicenter, open-label, non-randomized clinical trial, the use of COAGADEX in routine prophylaxis of bleeding episodes was evaluated in nine children aged less than 12 years of age. The mean age was 7.3 (range 2.6 to 11.9) years. Eight subjects had severe FX deficiency and the other had moderate deficiency. Four subjects were between 0 and 5 years of age and five were between 6 and 11 years of age inclusive. The majority of subjects were Asian (7; 77.8%) and the remainder were Caucasian/White (2; 22.2%). After the first dose of COAGADEX 50 IU/kg, given at a rate not exceeding 3 mL/minute, all subjects underwent a 30-minute post-dose incremental recovery assessment. Routine prophylaxis was started on Day 2 or 3 with unit doses of 40-50 IU/kg and during the first 6 weeks trough levels of Factor X were measured to adjust the dosage regimen to maintain a trough level of at least 5 IU/dL. At the end of the study (at least 6 months and at least 50 exposure days) a repeat 30-minute incremental recovery was performed. A total of 537 (mean 59.7 per subject) prophylactic infusions were administered. The median prophylactic dose per infusion per subject was 39.60 IU/kg (mean 38.76 IU/kg), and ranged from 18.0 to 47.3 IU/kg. Median and mean doses per infusion in the four children less than 6 years of age were both 40.1 IU/kg (95% CI 30.70, 49.57) and in the five children 6 to 11 years of age inclusive, median dose was 39.6 IU/kg and mean dose was 37.7 IU/kg (95% CI: 23.42, 51.91). The median dosing interval for all of the nine children was 3 days (range 2 to 8 days). Investigators' assessment following 6 months of routine prophylaxis was rated excellent in all 9 subjects; excellent was defined as 'no minor or major bleeds occurred during the study period' or 'lower frequency of bleeds than expected, given subject's medical/treatment history'. In addition, 22 infusions were given to treat a bleed, equivalent to 2.1 bleeds per subject per year. One subject had three episodes of epistaxis and the other bleeds were due to trauma or menorrhagia. All bleeds were treated with a single infusion; the median and mean doses per subject were both 31.7 IU/kg (range 24.6 to 38.8 IU/kg) and all recorded efficacy ratings were categorized as 'excellent' i.e. Overt bleed: bleeding stopped within 12 hours with a single dose; Menorrhagic bleed: no additional doses required; Covert bleeds: there were none in this study.

On-demand Treatment and Control of Bleeding Episodes

In a multicenter, open-label, non-randomized clinical trial to evaluate the pharmacokinetics, safety and efficacy of COAGADEX, 16 subjects with moderate to severe hereditary Factor X deficiency (FX:C < 5 IU/dL) received a dose of 25 IU/kg COAGADEX to treat spontaneous, traumatic and menorrhagic bleeding episodes. If hemostasis was not achieved with a single dose of COAGADEX, additional doses could be given until the bleed stopped. Subjects could also continue with treatment after the bleed had stopped to reduce the risk of recurrence of a given bleed. Subjects were aged 12 to 58 years, including 6 pediatric subjects aged 12 to 17 years. Six subjects were male, 10 were female, and 12 were Caucasian.

The efficacy of COAGADEX in treating bleeding episodes was assessed by the subject and/or investigator for each new bleeding episode, using a bleed-specific ordinal rating scale of excellent, good, poor and unassessable for each type of bleed (overt, covert or menorrhagic). Overt bleed: 'excellent' if bleeding stopped within 12 hours with a single dose; 'good' if within 24 hours with ≤2 doses. Covert bleed: 'excellent' if bleeding stopped within 48 hours with 1 or 2 doses; 'good' if within 48 hours with ≤3 doses. Menorrhagic bleed: 'excellent' if ≤2 doses within 48 hours; 'good' if 2 doses over >48 hours. Each bleed was reviewed by a Data Review Committee for its suitability for the efficacy evaluation. Of the 208 bleeding episodes treated with COAGADEX, 187 bleeding episodes in 15 subjects were evaluated for efficacy. Of these 187 bleeding episodes, 79 (42%) occurred spontaneously, 47 (25%) were traumatic and 61 (33%) were menorrhagic. Seventy three (39%) were mucosal in origin, 63 (34%) were joint bleeds, 26 (14%) were muscle bleeds, and 25 (13%) were located elsewhere.

Ninety eight (53%) were major bleeding episodes, and 88 (47%) were minor bleeds (one bleed not assessed). COAGADEX was considered to be good (7%) or excellent (91%) in treating 98% of bleeding episodes. Of the 187 bleeding episodes in the efficacy analysis, a total of 155 bleeds (83%) were treated with one infusion, 28 bleeds (15%) with two infusions, 3 bleeds (2%) with three infusions and 1 bleed (0.5%) with four infusions. The mean dose per infusion and total dose of COAGADEX were 25.4 IU/kg and 30.4 IU/kg, respectively. Four bleeding episodes in two subjects were considered treatment failures.

The recommended dose of 25 IU/kg COAGADEX to treat a bleed was maintained during the study for 14 of the 16 subjects. The other two subjects used doses up to 30 IU/kg and 33 IU/kg.

Perioperative Management of Bleeding

In two multicenter, open-label, non-randomized clinical trials, subjects requiring surgery received a pre-surgical COAGADEX dose to raise plasma Factor X levels to 70-90 IU/dL, followed by post-surgical doses as necessary to maintain plasma Factor X levels at a minimum of 50 IU/dL until the subject was no longer at risk of bleeding due to surgery. The safety and efficacy of COAGADEX for perioperative management was evaluated in five subjects aged 14 to 59 years with mild, moderate or severe hereditary Factor X deficiency, who underwent a total of seven surgical procedures.

For all surgical procedures, COAGADEX was assessed as excellent by the investigator for overall hemostatic control of peri-operative blood loss. Assessment of hemostatic efficacy was based on parameters including: blood loss during surgery, blood transfusion requirements, bleeding episodes and hemoglobin levels. An excellent score required the achievement of outcomes in these parameters similar to patients without a bleeding disorder. For major surgeries, a median of 13 infusions (range 2 to 15 infusions) and a median cumulative dose of 181 IU/kg (range 45 to 210 IU/kg) were required to maintain hemostasis. For minor surgeries, a median of 2.5 infusions (range 1 to 4 infusions) and a median cumulative dose of 89 IU/kg (range 51 to 127 IU/kg) were required to maintain hemostasis.

One subject had insertion of a central venous access device (Portacath) and was given 6 infusions of COAGADEX during 5 days, a total of 2,750 IU (27 IU/kg); there were no bleeding complications or safety concerns.

In a post-marketing registry study, 3 subjects (aged 21 to 30 years) with severe hereditary Factor X deficiency received a total of 10 (mean 3.3) doses of COAGADEX for perioperative hemostatic cover. The median initial (pre-surgery) dose was 44.3 IU/kg (mean 40.6; range 28.6 to 48.9). A median of 4 (range 1 to 5) infusions was administered, with median cumulative dose 110.2 IU/kg (range 28.6 to 171.8). All three subjects achieved excellent hemostatic efficacy outcomes.

16 HOW SUPPLIED/STORAGE AND HANDLING

How Supplied

COAGADEX is supplied in single-dose glass vials containing a nominal (approximate) 250 IU or 500 IU (approximately 100 IU/mL after reconstitution) of Factor X activity, packaged with 2.5 mL or 5 mL of Sterile Water for Injection, respectively, and a Mix2Vial transfer device.

The vials are closed with a synthetic rubber stopper. The stopper is not made with natural rubber latex. The stopper is secured with an aluminum overseal with a flip-off polypropylene cap.

Strength | Kit NDC Number
250 IU Range | 64208-7752-1
500 IU Range | 64208-7753-1

Storage and Handling

- Store COAGADEX in its original package to protect it from light.
- Store the COAGADEX package in a refrigerator or at room temperature at 36°F to 86°F (2°C to 30°C). Do not freeze.
- Do not use COAGADEX or the Sterile Water for Injection after the expiration date printed on the vial and carton labels.
- Use reconstituted COAGADEX within one hour of reconstitution.
- Do not use COAGADEX if the reconstituted solution is cloudy or contains any particles.

17 PATIENT COUNSELING INFORMATION

- Advise the patients to read the FDA-approved patient labeling (Patient Information and Instructions for Use).
- Inform patients to immediately report the following early signs and symptoms of hypersensitivity reactions to their healthcare professional: angioedema, infusion site inflammation (e.g. burning, stinging, erythema), chills, cough, dizziness, fever, flushing, generalized urticaria, headache, hives, hypotension, lethargy, musculoskeletal pains, nausea, pruritus, rash, restlessness, tachycardia, tightness of the chest, tingling, vomiting, wheezing [see Warnings and Precautions (5.1)].
- Inform patients that the development of inhibitors to Factor X is a possible complication of treatment with COAGADEX. Advise the patients to contact their healthcare provider for further treatment and/or assessment if they experience a lack of clinical response to COAGADEX because this may be a manifestation of an inhibitor [see Warnings and Precautions (5.2)].
- Inform patients that COAGADEX is made from human plasma and may contain infectious agents that can cause diseases. While the risk that COAGADEX can transmit an infection has been reduced by screening plasma donors for prior exposure, testing donated plasma, and inactivating or removing certain viruses during manufacturing, patients should report any symptoms that concern them [see Warnings and Precautions (5.3)].

Manufactured by:
Bio Products Laboratory Ltd.,
Dagger Lane,
Elstree,
Borehamwood,
WD6 3BX,
United Kingdom.

U.S. Distributor:
BPL USA, Inc.,
302 East Pettigrew Street,
Suite C-190,
Durham, NC 27701
USA

U.S. License No: 1811

COAGADEX® is a registered trade mark of Bio Products Laboratory Limited. Mix2Vial™ is a trade mark of West Pharmaceutical services.

Version 6

Patient Information

COAGADEX® (co-ag-a-dex)
Coagulation Factor X (Human)

This Patient Information leaflet summarizes important information about COAGADEX. Please read it carefully before using COAGADEX and each time you get a refill, as there may be new information. This Patient Information does not take the place of talking with your healthcare provider about your medical condition or treatment, and it does not include all of the important information about COAGADEX. If you have any questions about COAGADEX after reading this information, ask your healthcare provider.

What is the most important information I need to know about COAGADEX?

Do not attempt to do an infusion yourself unless you have been taught how by your healthcare provider or hemophilia center.

You must carefully follow your healthcare provider's instructions regarding the dose and schedule for infusing COAGADEX so that your treatment will work best for you.

What is COAGADEX?

COAGADEX is a medicine given as an infusion into the vein to replace the clotting factor that is missing in people with Factor X deficiency. Factor X deficiency is an inherited bleeding disorder that prevents blood from clotting normally.

COAGADEX is used to treat, control or reduce bleeding in patients with hereditary Factor X deficiency.

Your healthcare provider may give you COAGADEX when you have surgery.

Who should not use COAGADEX?

You should not use COAGADEX if you are allergic (hypersensitive) to any of the ingredients in COAGADEX.

Tell your healthcare provider if you are pregnant or breast-feeding because COAGADEX may not be right for you.

What should I tell my healthcare provider before I use COAGADEX?

You should tell your healthcare provider if you:

- Have or have had any medical problems
- Have any allergies
- Take any prescription and non-prescription medicines, including over-the-counter medicines, supplements or herbal medicines
- Are breast-feeding. It is not known if COAGADEX passes into your milk and if it can harm your baby
- Are pregnant or planning to become pregnant. It is not known if COAGADEX may harm your unborn baby
- Have been told you have inhibitors to Factor X

How should I use COAGADEX?

You get COAGADEX as an infusion into your vein.

You may infuse COAGADEX at a hemophilia treatment center, at your healthcare provider's office or in your home. You should be trained on how to do infusions by your healthcare provider or hemophilia treatment center. Many people with coagulation factor deficiencies learn to infuse their treatment by themselves or with the help of a family member or caregiver.

Your healthcare provider will tell you how much COAGADEX to use based on your weight, the severity of your Factor X deficiency, and where you are bleeding from.

You may need blood tests done after using COAGADEX to be sure that the level of Factor X in your blood is high enough to clot your blood.

Call your healthcare provider right away if your bleeding does not stop after using COAGADEX.

What are the possible side-effects of COAGADEX?

You can have an allergic reaction to COAGADEX.

Stop treatment and call your healthcare provider right away if you have any of the following symptoms: difficulty breathing, chest tightness, swelling of the face, rash or hives.

Common side effects of COAGADEX are infusion site redness, infusion site pain, tiredness, and back pain.

Your body can also make antibodies, called "inhibitors," against COAGADEX, which may stop COAGADEX from working properly. Your healthcare provider may give you blood tests to check for inhibitors.

These are not all of the possible side effects of COAGADEX. Tell your healthcare provider about any side effects that bother you or do not go away.

What are the COAGADEX dosage strengths?

COAGADEX is packaged with a suitable volume (2.5 mL or 5 mL) of Sterile Water for Injection, and one Mix2Vial transfer device.

COAGADEX comes in two different dosage strengths:

Approximately 250 International Units (IU) – to be reconstituted with 2.5 mL of sterile water.

Approximately 500 International Units (IU) - to be reconstituted with 5 mL of sterile water.

The actual strength will be printed on the vial label and on the box. Once dissolved, the concentrations in these two vials will be the same, 100 IU per mL.

Always check the actual dosage printed on the label to make sure you are using the vial size prescribed by your healthcare provider.

Always check the expiration date printed on the box. Do not use the product after the expiration date printed on the box.

How do I store COAGADEX?

- Keep COAGADEX in its original package to protect it from light.
- Store COAGADEX in a refrigerator (not below 36°F [2°C]) or at room temperature (not to exceed 86°F [30°C]). Do not freeze.

What else should I know about COAGADEX?

Medicines are sometimes prescribed for purposes other than those listed here. Do not use COAGADEX for a condition for which it is not prescribed.

Do not share COAGADEX with other people, even if they have the same symptoms or condition that you have.

For further information or if you have any questions about COAGADEX, please contact BPL Inc. at the address below or through medinfo@bpl-us.com.

U.S. Distributor:
BPL USA, Inc.,
302 East Pettigrew Street,
Suite C-190,
Durham, NC 27701,
USA

Manufactured by:
Bio Products Laboratory Ltd.,
Dagger Lane, Elstree,
Borehamwood, WD6 3BX,
United Kingdom.
U.S. License No: 1811

Version 6

Instructions for Use

COAGADEX® (co-ag-a-dex)
Coagulation Factor X (Human)

Important: Do not attempt to give an infusion to yourself unless you have been taught how to by your healthcare provider or hemophilia center.

Always follow the specific instructions given by your healthcare provider. The steps listed below are general guidelines for using COAGADEX. If you are unsure of the procedures, please call your healthcare provider before using.

Your healthcare provider will prescribe the dose and when to use COAGADEX. Contact your healthcare provider right away if you accidentally take more than the prescribed dose.

Your healthcare provider may need to take blood tests from time to time.

Talk to your healthcare provider before traveling. Plan to take enough COAGADEX for your treatment during this time.

Dispose of all materials, including any leftover reconstituted COAGADEX product, in an appropriate container.

How should I dissolve COAGADEX before use?

COAGADEX must be dissolved in the sterile water provided with the product using the provided transfer device called Mix2Vial™.

See below for step-by-step instructions for reconstituting COAGADEX.

 | Step 1; - Bring the vials of COAGADEX and sterile water to room temperature before mixing. - Remove the cap from the vial of COAGADEX and clean the top of the stopper with an alcohol swab. - Repeat this step with the vial of sterile water.; Step 2; - Peel back the top of the Mix2Vial package but leave the device in the package. |  | Step 5; - The sterile water will be pulled into the vial of COAGADEX by the vacuum contained within it. - Gently swirl the vial to make sure the powder is thoroughly mixed. Do not shake the vial. - A clear or slightly pearl-like solution should be obtained, usually in less than 1 minute (5 minutes maximum).; Note: If the water is not pulled into the vial of COAGADEX. This indicates a loss of vacuum in the vial. Do not use the product.
 | Step 3; - Place the blue end of the Mix2Vial on the sterile water vial and push straight down until the spike penetrates the rubber stopper and snaps into place. - Remove the plastic outer packaging from the Mix2Vial and discard it. Do not touch the exposed end of the device. |  | Step 6; - Separate the empty sterile water vial and blue part from the clear part by unscrewing counter-clockwise.; Step 7; - Draw air into the syringe by pulling the plunger to the required volume of sterile water added. - Connect the syringe to the clear part of the Mix2Vial. - Push the air in the syringe into the vial.
 | Step 4; - Turn the sterile water vial upside down with the device still attached. - Place the clear end of the Mix2Vial on the product vial and push straight down until the spike penetrates the rubber stopper and snaps into place. |  | Step 8; - Immediately invert the COAGADEX vial. The solution will be drawn into the syringe. - Disconnect the filled syringe from the device. - Use the product immediately or within one hour of reconstitution. Do not store the reconstituted product.; Note: If there are any particles in the syringe, or if the solution is cloudy, or if a gel or clot forms, contact the manufacturer to report the batch number printed on the vial.

If you have to use more than one vial of COAGADEX to make up your dose, repeat steps 1 to 5 to reconstitute each vial and draw up all of the solution into one syringe for your infusion. You must use a new Mix2Vial to draw the contents of each vial up into the plastic syringe.

How do I infuse COAGADEX?

Inspect the solution before infusion. Do not use if there are any particles in the syringe, or if the solution is cloudy, or if a gel or clot forms.

Do not add the solution to any other fluids and do not mix it together with any other medicine.

To infuse the medicine:

- Attach a suitable needle to the syringe containing COAGADEX solution.
- Inject the dose at a suggested rate of 10 mL/min, but no more than 20 mL/min into your vein.

After infusing the medicine:

After infusion, safely dispose of the needle, tubing, syringe, any unused COAGADEX and other waste materials. Record the infusion in your infusion tracker or calendar.

Important: Contact your healthcare provider or local hemophilia treatment center if you experience any problems.

COAGADEX® is a registered trade mark of Bio Products Laboratory Limited. Mix2Vial™ is a trade mark of West Pharmaceutical services.

This Instructions for Use has been approved by the U.S. Food and Drug Administration.

Manufactured by: Bio Products Laboratory Ltd., Dagger Lane, Elstree, Borehamwood, WD6 BX, United Kingdom.

U.S. License No: 1811
Revised 03/2023

Version 6

PRINCIPAL DISPLAY PANEL - 250 IU Kit Carton

NDC: 64208-7752-1

250 IU Range

Coagulation Factor X
(Human)

Coagadex®

LYOPHILIZED POWDER FOR SOLUTION
FOR INJECTION

FOR INTRAVENOUS USE ONLY

Rx ONLY

Manufactured by:
Bio Products Laboratory Ltd.,
Dagger Lane, Elstree, Borehamwood, WD6 3BX,
United Kingdom
U.S. License No. 1811

Bio Products Laboratory

PRINCIPAL DISPLAY PANEL - 250 IU Vial Label

Coagulation Factor X
(Human)
Coagadex®

250 IU Range

- FOR INTRAVENOUS USE ONLY.
- Read enclosed package insert before use.
- Rx only.
- Store between 36°F – 86°F (2°C – 30°C).
- DO NOT FREEZE.

NDC: 64208-7754-1

FXRNUS2L

PRINCIPAL DISPLAY PANEL - 2.5 mL Vial Label

Sterile Water
for Injection

2.5 mL

Store between 36°F – 86°F (2°C – 30°C).
Do not freeze.
Do not use unless clear.
NDC: 64208-7755-1

Bio Products Laboratory Ltd., Elstree,
WD6 3BX, United Kingdom
WWBNUS2L

PRINCIPAL DISPLAY PANEL - 500 IU Kit Carton

NDC: 64208-7753-1

500 IU Range

Coagulation Factor X
(Human)

Coagadex®

LYOPHILIZED POWDER FOR SOLUTION
FOR INJECTION

FOR INTRAVENOUS USE ONLY

Rx ONLY

Manufactured by:
Bio Products Laboratory Ltd.,
Dagger Lane, Elstree, Borehamwood, WD6 3BX,
United Kingdom
U.S. License No. 1811

Bio Products Laboratory

PRINCIPAL DISPLAY PANEL - 500 IU Vial Label

Coagulation Factor X
(Human)
Coagadex®

500 IU Range

- FOR INTRAVENOUS USE ONLY.
- Read enclosed package insert before use.
- Rx only.
- Store between 36°F – 86°F (2°C – 30°C).
- DO NOT FREEZE.

NDC: 64208-7756-1

FXSNUS2L

PRINCIPAL DISPLAY PANEL - 5 mL Vial Label

Sterile Water
for Injection

5 mL

Store between 36°F – 86°F (2°C – 30°C).
Do not freeze.
Do not use unless clear.
NDC: 64208-7755-2

Bio Products Laboratory Ltd., Elstree,
WD6 3BX, United Kingdom
WWENUS2L